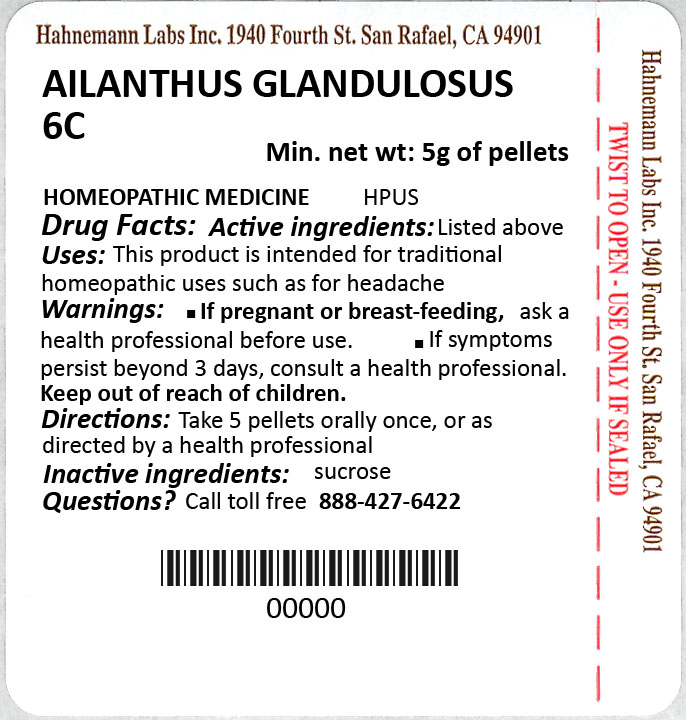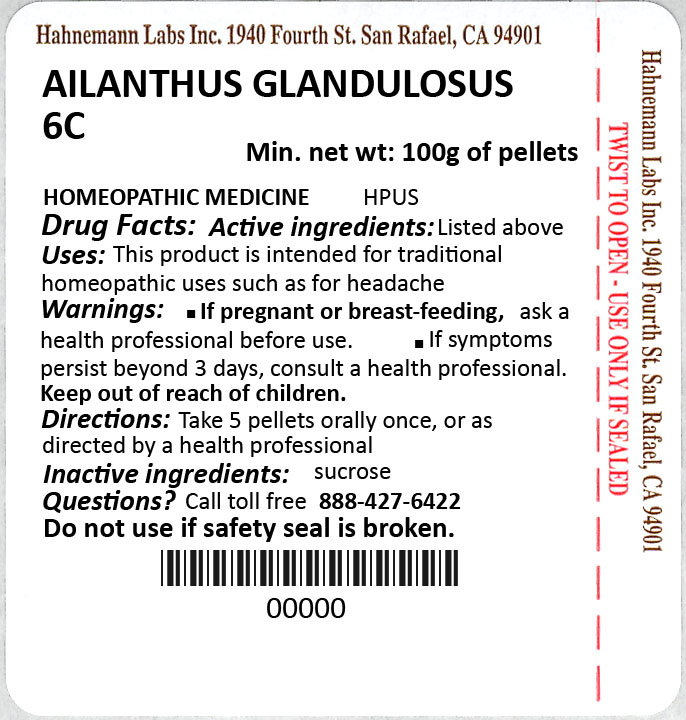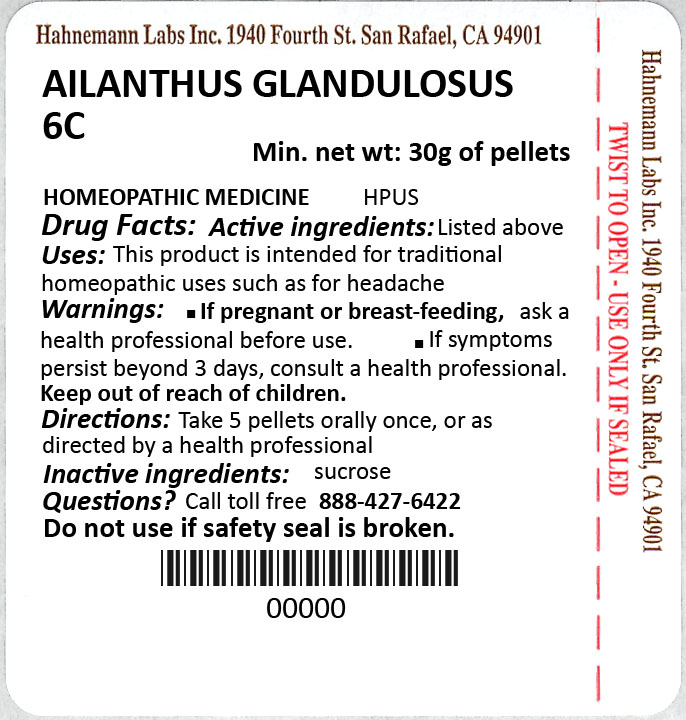 DRUG LABEL: Ailanthus glandulosa
NDC: 63545-335 | Form: PELLET
Manufacturer: Hahnemann Laboratories, Inc.
Category: homeopathic | Type: HUMAN OTC DRUG LABEL
Date: 20200106

ACTIVE INGREDIENTS: AILANTHUS ALTISSIMA FLOWERING TWIG 6 [hp_C]/1 1
INACTIVE INGREDIENTS: SUCROSE

Single label image contains content for sections 1-14.

\